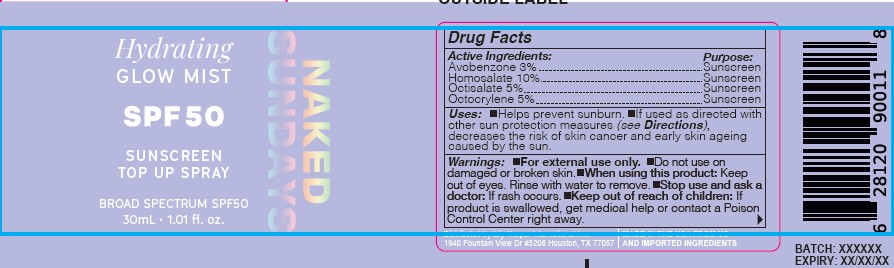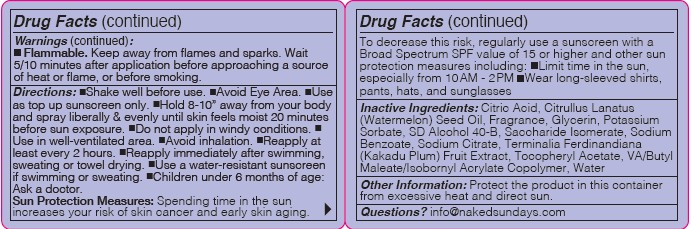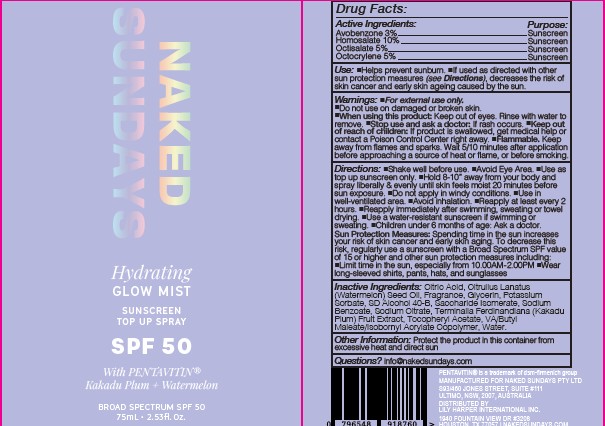 DRUG LABEL: Hydrating Glow Mist with  Pentavitin
NDC: 81104-017 | Form: SPRAY
Manufacturer: NAKED SUNDAYS PTY LTD
Category: otc | Type: HUMAN OTC DRUG LABEL
Date: 20260127

ACTIVE INGREDIENTS: AVOBENZONE 3 g/100 mL; OCTOCRYLENE 5 g/100 mL; OCTISALATE 5 g/100 mL; HOMOSALATE 10 g/100 mL
INACTIVE INGREDIENTS: ALPHA-TOCOPHEROL ACETATE; WATERMELON SEED OIL; GLYCERIN; KAKADU PLUM; SODIUM CITRATE; SODIUM BENZOATE; CITRIC ACID; POTASSIUM SORBATE; ALCOHOL; SACCHARIDE ISOMERATE; WATER

Hydrating Glow Mist with Pentavitin

Active Ingredients

Avobenzone 3%

Homosalate 10%

Octisalate 5%

Octocrylene 5%

Purpose

Sunscreen

Uses

- helps prevent sunburn
- if used as directed with other sun protection measures (see directions), decreases the risk of skin cancer and early skin aging caused by the sun

Warnings

- For external use only.
- Flammable: Keep away from flames and sparks. Wait 5/10 minutes after application before approaching a source of heat or flame, or before smoking

Do not use

on damaged or broken skin

When using this product

Keep out of eyes. Rinse with water to remove

Stop use and ask a doctor

if rash occurs

Keep out of reach of children

If product is swallowed, get medical help or contact a Poison Control Center right away

Directions

- shake well before use
- Avoid eye area
- use as top up sunscreen only
- hold 8-10" away from your body and spray liberally & evenly until skin feels moist 20 minutes before sun exposure
- Do not apply in windy conditions
- Use in a well-ventilated area
- Avoid inhalation
- Reapply at least every 2 hours
- Reapply immediately after swimming, sweating or towel drying.
- Use a water resistant sunscreen if swimming or sweating.
- Children under 6 months of age: ask a doctor
- Sun Protection Measures: Spending time in the sun increases your risk of skin cancer and early skin aging. To decrease this risk regularly use a sunscreen with a Broad Spectrum SPF value of 15 or higher and other sun protection measures including:
- Limit time in the sun, especially from 10am - 2pm
- Wear long-sleeved shirts, pants, hats, and sunglasses

Inactive Ingredients

Citric Acid, Citrullus Lanatus (Watermelon) Seed Oil, Fragrance, Glycerin, Potassium Sorbate, SD Alcohol 40-B, Saccharide Isomerate, Sodium Benzoate, Sodium Citrate, Terminalia Ferdinandiana (Kakadu Plum) Fruit Extract, Tocopheryl Acetate, VA/Butyl Maleate/Isobornyl Acrylate Copolymer, Water

Other Information

Protect the product in this container from excessive heat and direct sun

Questions?

info@nakedsundays.com